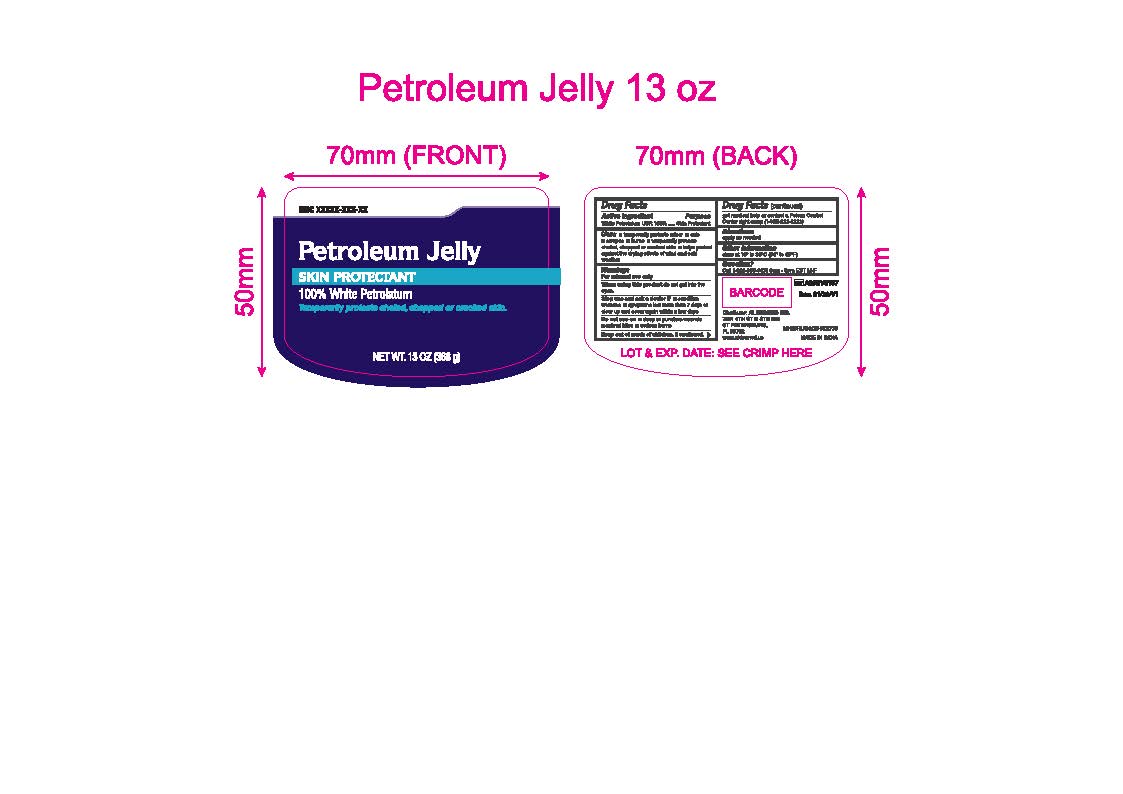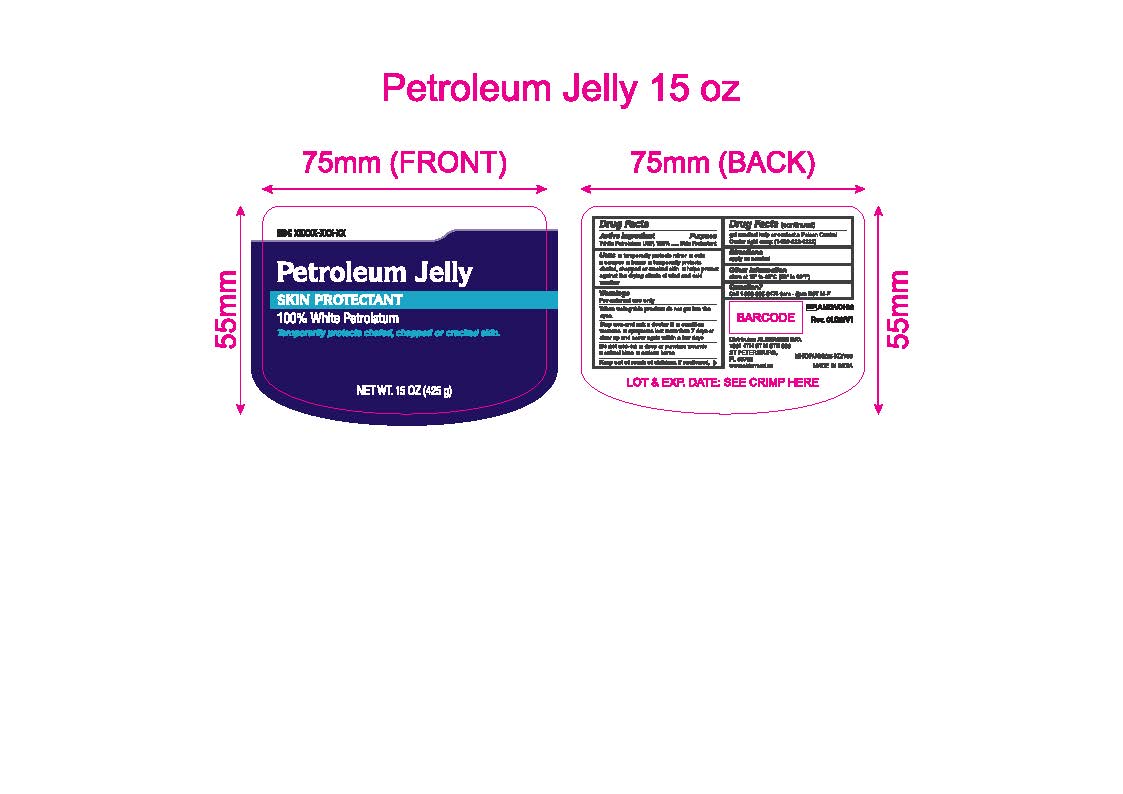 DRUG LABEL: Petroleum Jelly
NDC: 87236-009 | Form: JELLY
Manufacturer: Aldermed Inc.
Category: otc | Type: HUMAN OTC DRUG LABEL
Date: 20260212

ACTIVE INGREDIENTS: WHITE PETROLATUM 1 g/1 g
INACTIVE INGREDIENTS: WATER

Petroleum Jelly

Active ingredient

White petrolatum USP 100%

Purpose

Skin protectant

Uses

temporarily protects minor

- cuts
- scrapes
- burns
- temporarily protects and chafed, chapped or cracked skin
- helps prevent against the drying effects of wind and cold weather

Warnings

For external use only

Do not use on

- deep or puncture wounds
- animal bites
- serious burns

When using this product

- do not get into eyes

Stop use and ask a doctor if

- condition worsens
- symptoms last for more than 7 days or clear up and occur again within a few days

Keep out of reach of children.

In swallowed, get medical help or contact a Poison Control Center right away. (1-800-222-1222)

Directions

apply as needed

Other information

- store at 15-30 C (59-86F)

Inactive ingredients

none

Questions or comments?

Call 1-833-605-84-74 9am-5 pm EST M-F

Distributror

Distributor:
ALDERMED INC.
7901 4TH ST N STE 300 ST PETERSBURG, FL 33702
www.aldermed.us MADE IN INDIA MH/DRUGS/25-KD/739